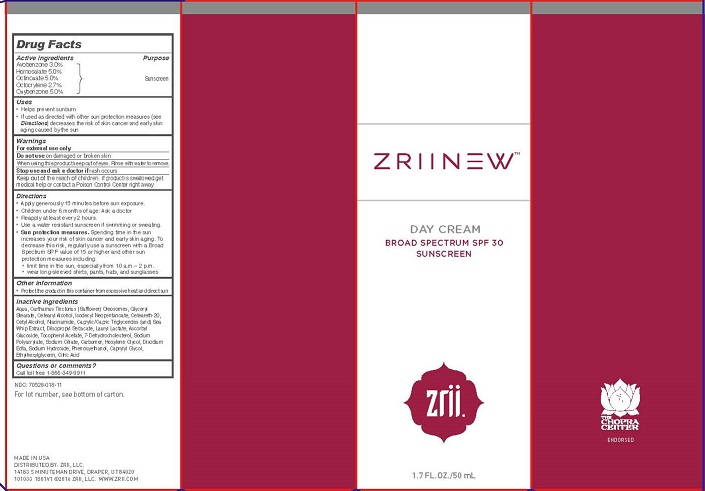 DRUG LABEL: ZRII NEW DAY
NDC: 70528-018 | Form: CREAM
Manufacturer: ZRII, LLC
Category: otc | Type: HUMAN OTC DRUG LABEL
Date: 20160705

ACTIVE INGREDIENTS: AVOBENZONE 3 g/100 mL; HOMOSALATE 5 g/100 mL; OCTINOXATE 5 g/100 mL; OCTOCRYLENE 2.7 g/100 mL; OXYBENZONE 5 g/100 mL
INACTIVE INGREDIENTS: WATER; SAFFLOWER OIL; GLYCERYL MONOSTEARATE; CETOSTEARYL ALCOHOL; ISODECYL NEOPENTANOATE; CETEARETH-22; CETYL ALCOHOL; NIACINAMIDE; MEDIUM-CHAIN TRIGLYCERIDES; PSEUDOPTEROGORGIA ELISABETHAE; DIISOPROPYL SEBACATE; LAURYL LACTATE; ASCORBYL GLUCOSIDE; .ALPHA.-TOCOPHEROL ACETATE; 7-DEHYDROCHOLESTEROL; SODIUM POLYACRYLATE (8000 MW); SODIUM CITRATE; CARBOMER 940; HEXYLENE GLYCOL; EDETATE DISODIUM; SODIUM HYDROXIDE; PHENOXYETHANOL; CAPRYLYL GLYCOL; ETHYLHEXYLGLYCERIN; ANHYDROUS CITRIC ACID

ACTIVE INGREDIENTS

Avobenzone 3.0%
Homosalate 5.0%
Octinoxate 5.0%
Octocrylene 2.7%
Oxybenzone 5.0%

PURPOSE

SUNSCREEN

USES

- Helps prevent sunburn

- If used as directed with other sun protection measures (see Directions) decreases the risk of skin cancer and early skin aging caused by the sun

WARNINGS

For external use only
Do not use on damaged or broken skin
When using this product keep out of eyes. Rinse with water to remove.
Stop use and ask a doctor if rash occurs

KEEP OUT OF REACH OF CHILDREN

Keep out of the reach of children. If product is swallowed get medical help or contact a Poison Control Center right away.

DIRECTIONS

- Apply generously 15 minutes before sun exposure.
- Children under 6 months of age: Ask a doctor
- Reapply at least every 2 hours.
- Use a water resistant sunscreen if swimming or sweating.
- Sun protection measures. Spending time in the sun increases your risk of skin cancer and early skin aging. To decrease this risk, regularly use a sunscreen with a Broad Spectrum SPF value of 15 or higher and other sun protection measures including:
- limit time in the sun, especially from 10 a.m.– 2 p.m.
- wear long-sleeved shirts, pants, hats, and sunglasses

OTHER INFORMATION

- Protect the product in this container from excessive heat and direct sun

INACTIVE INGREDIENTS

Aqua, Carthamus Tinctorius (Safflower) Oleosomes, Glyceryl Stearate, Cetearyl Alcohol, Isodecyl Neopentanoate, Ceteareth-20, Cetyl Alcohol, Niacinamide, Caprylic/Capric Triglycerides (and) Sea Whip Extract, Diisopropyl Sebacate, Lauryl Lactate, Ascorbyl Glucoside, Tocopheryl Acetate, 7-Dehydrocholesterol, Sodium Polyacrylate, Sodium Citrate, Carbomer, Hexylene Glycol, Disodium Edta, Sodium Hydroxide, Phenoxyethanol, Caprylyl Glycol, Ethylhexylglycerin, Citric Acid

QUESTIONS OR COMMENTS?

Call toll free 1-866-349-9911